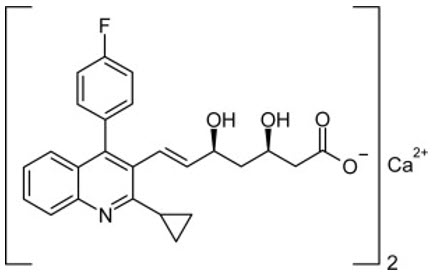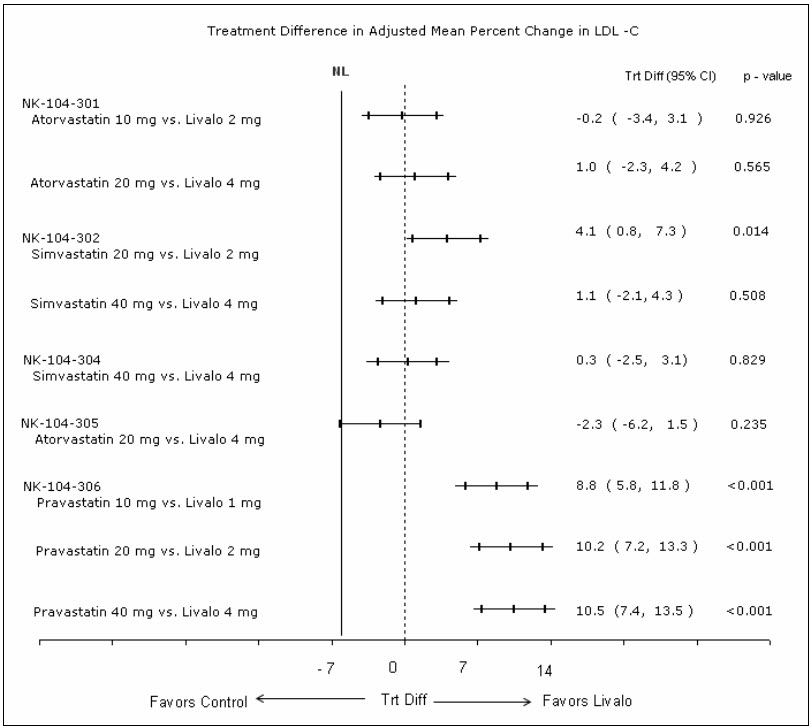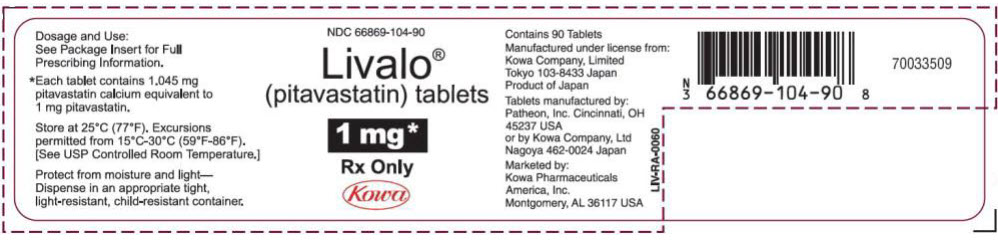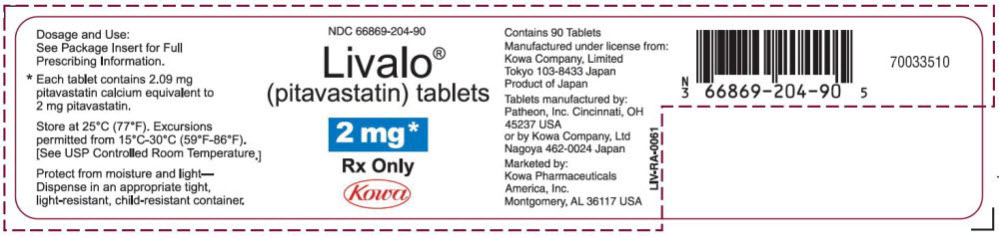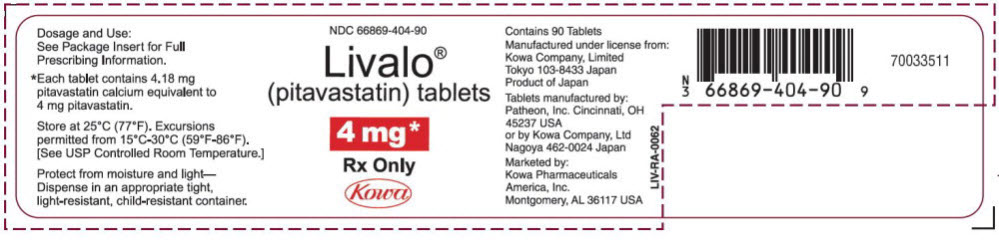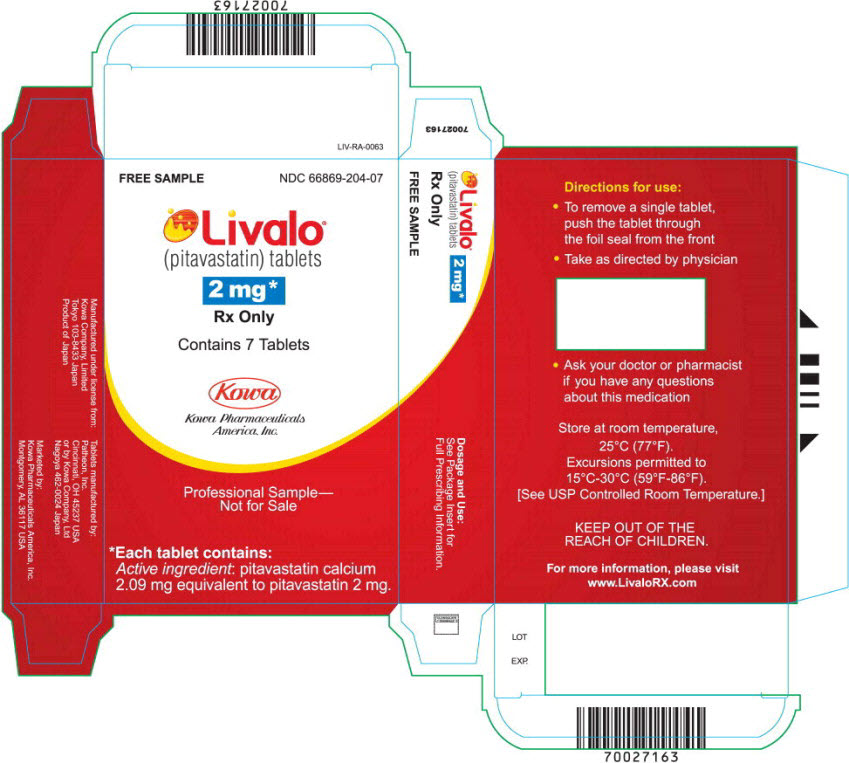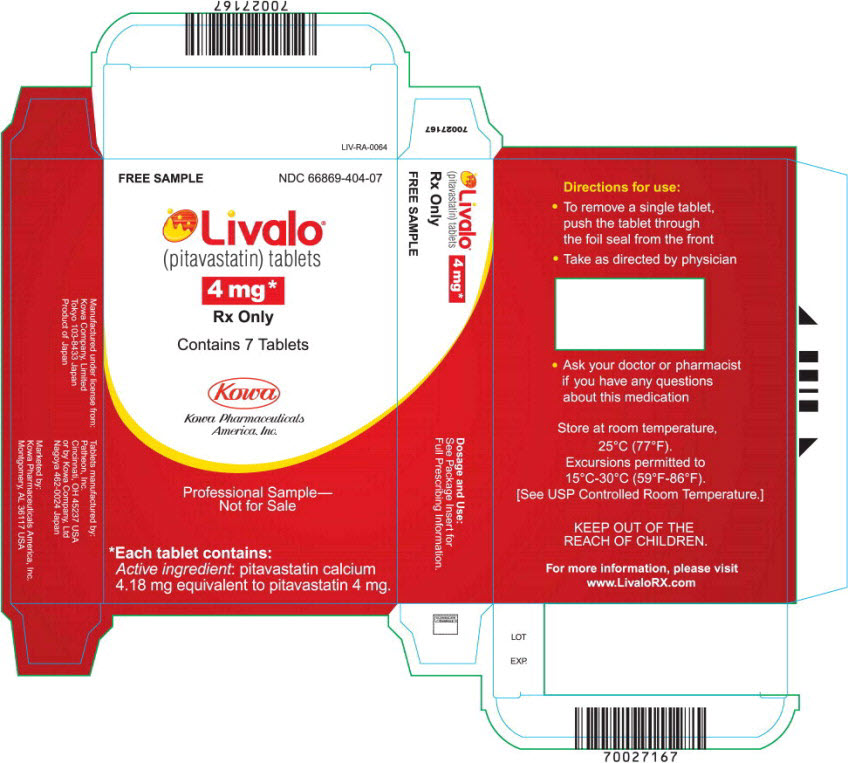 DRUG LABEL: Livalo
NDC: 66869-104 | Form: TABLET, FILM COATED
Manufacturer: Kowa Pharmaceuticals America, Inc.
Category: prescription | Type: HUMAN PRESCRIPTION DRUG LABEL
Date: 20260209

ACTIVE INGREDIENTS: PITAVASTATIN CALCIUM 1.045 mg/1 1
INACTIVE INGREDIENTS: LACTOSE MONOHYDRATE; LOW-SUBSTITUTED HYDROXYPROPYL CELLULOSE, UNSPECIFIED; HYPROMELLOSE, UNSPECIFIED; MAGNESIUM ALUMINOMETASILICATE TYPE IB; MAGNESIUM STEARATE; TITANIUM DIOXIDE; TRIETHYL CITRATE; SILICON DIOXIDE

HIGHLIGHTS OF PRESCRIBING INFORMATION

These highlights do not include all the information needed to use LIVALO® safely and effectively. See full prescribing information for LIVALO.
LIVALO (pitavastatin) tablets, for oral use
Initial U.S. Approval: 2009

RECENT MAJOR CHANGES

Contraindications, Pregnancy and Lactation (4) | Removed 11/2022
Warnings and Precautions, Immune-Mediated Necrotizing Myopathy (5.2) | 11/2022

1 INDICATIONS AND USAGE

LIVALO is a HMG-CoA reductase inhibitor (statin) indicated as an adjunct to diet to reduce low-density lipoprotein cholesterol (LDL-C) in: (1)

- Adults with primary hyperlipidemia.
- Adults and pediatric patients aged 8 years and older with heterozygous familial hypercholesterolemia (HeFH).

2 DOSAGE AND ADMINISTRATION

- Take orally once daily with or without food at the same time each day. (2.1)
- For patients requiring a high-intensity statin or are unable to achieve their LDL-C goal receiving LIVALO 4 mg daily, prescribe alternative LDL-C-lowering treatment. (2.1)
- Assess LDL-C when clinically appropriate, as early as 4 weeks after initiation of LIVALO, and adjust the dosage if necessary. (2.1)
- Recommended dosage is 2 mg to 4 mg once daily. Maximum recommended dosage is 4 mg once daily. (2.2)
- Recommended starting dosage for patients with moderate and severe renal impairment and end-stage renal disease on hemodialysis is 1 mg once daily. Maximum recommended dosage is 2 mg once daily. (2.3)
- See full prescribing information for LIVALO dosage modifications due to drug interactions. (2.4)

3 DOSAGE FORMS AND STRENGTHS

Tablets: 1 mg, 2 mg, and 4 mg (3)

4 CONTRAINDICATIONS

- Cyclosporine (4, 7)
- Active liver failure or decompensated cirrhosis (4, 5.3)
- Hypersensitivity to pitavastatin or any excipients in LIVALO (4)

5 WARNINGS AND PRECAUTIONS

- Myopathy and Rhabdomyolysis: Risk factors include age 65 or greater, uncontrolled hypothyroidism, renal impairment, concomitant use with certain other drugs, and higher LIVALO dosage. Discontinue LIVALO if markedly elevated CK levels occur or myopathy is diagnosed or suspected. Temporarily discontinue LIVALO in patients experiencing an acute or serious condition at high risk of developing renal failure secondary to rhabdomyolysis. Inform patients of the risk of myopathy and rhabdomyolysis when starting or increasing the LIVALO dosage. Instruct patients to promptly report unexplained muscle pain, tenderness or weakness particularly if accompanied by malaise or fever. (5.1, 7, 8.5, 8.6)
- Immune-Mediated Necrotizing Myopathy (IMNM): Rare reports of IMNM, an autoimmune myopathy, have been reported. Discontinue LIVALO if IMNM is suspected. (5.2)
- Hepatic Dysfunction: Increases in serum transaminases have occurred, some persistent. Rare reports of fatal and non-fatal hepatic failure have occurred. Consider testing liver enzymes before initiating therapy and as clinically indicated thereafter. If serious hepatic injury with clinical symptoms and/or hyperbilirubinemia or jaundice occurs, promptly discontinue LIVALO. (5.3)

6 ADVERSE REACTIONS

The most frequent adverse reactions (rate ≥ 2%) were myalgia, constipation, , diarrhea, back pain, and pain in extremity. (6)

To report SUSPECTED ADVERSE REACTIONS, contact Kowa Pharmaceuticals America, Inc. at 1-877-334-3464 or FDA at 1-800-FDA-1088 or www.fda.gov/medwatch.

7 DRUG INTERACTIONS

See full prescribing information for details regarding concomitant use of LIVALO with other drugs that increase the risk of myopathy and rhabdomyolysis. (2.4, 7)

8 USE IN SPECIFIC POPULATIONS

- Pregnancy: May cause fetal harm. (8.1)
- Lactation: Breastfeeding not recommended during treatment with LIVALO. (8.2)

FULL PRESCRIBING INFORMATION

1 INDICATIONS AND USAGE

LIVALO is indicated as an adjunct to diet to reduce low-density lipoprotein cholesterol (LDL-C) in:

- Adults with primary hyperlipidemia.
- Adults and pediatric patients aged 8 years and older with heterozygous familial hypercholesterolemia (HeFH).

2 DOSAGE AND ADMINISTRATION

2.1 Important Dosage and Administration Information

- Take LIVALO orally once daily with or without food at the same time each day.
- For patients that require a high-intensity statin or are unable to achieve their LDL-C goal receiving LIVALO 4 mg daily, prescribe alternative LDL-C-lowering treatment.
- Assess LDL-C when clinically appropriate, as early as 4 weeks after initiating LIVALO, and adjust the dosage if necessary.

2.2 Recommended Dosage for Adults and Pediatric Patients Aged 8 Years and Older

- The recommended dosage range of LIVALO is 2 mg to 4 mg daily.
- The maximum recommended dosage is LIVALO 4 mg once daily .

2.3 Recommended Dosage in Patients with Renal Impairment

- The recommended starting dosage for patients with moderate and severe renal impairment (estimated glomerular filtration rate 30 – 59 mL/minute/1.73 m^2 and 15 – 29 mL/minute/1.73 m^2, respectively) and patients with end-stage renal disease receiving hemodialysis is LIVALO 1 mg once daily. The maximum recommended dose for these patients is LIVALO 2 mg once daily [see Use in Specific Populations (8.5)].
- There are no dosage adjustment recommendations for patients with mild renal impairment.

2.4 Dosage Modifications Due to Drug Interactions

- In patients taking erythromycin, do not exceed LIVALO 1 mg once daily [see Drug Interactions (7)].
- In patients taking rifampin, do not exceed LIVALO 2 mg once daily [see Drug Interactions (7)].

3 DOSAGE FORMS AND STRENGTHS

Tablets:

- 1 mg: Round white tablet, debossed "KC" on one side and "1" on the other side.
- 2 mg: Round white tablet, debossed "KC" on one side and "2" on the other side.
- 4 mg: Round white tablet, debossed "KC" on one side and "4" on the other side.

4 CONTRAINDICATIONS

LIVALO is contraindicated in the following conditions:

- Concomitant use of cyclosporine [see Drug Interactions (7)].
- Acute liver failure or decompensated cirrhosis [see Warnings and Precautions (5.3)].
- Hypersensitivity to pitavastatin or any excipents in LIVALO. Hypersensitivity reactions including angioedema, rash, pruritus, and urticaria have been reported with LIVALO [see Adverse Reactions (6)].

5 WARNINGS AND PRECAUTIONS

5.1 Myopathy and Rhabdomyolysis

LIVALO may cause myopathy (muscle pain, tenderness, or weakness associated with elevated creatine kinase [CK]) and rhabdomyolysis. Acute kidney injury secondary to myoglobinuria and rare fatalities have occurred as a result of rhabdomyolysis in patients treated with statins, including LIVALO.

Risk Factors for Myopathy

Risk factors for myopathy include age 65 years or greater, uncontrolled hypothyroidism, renal impairment, concomitant use of certain drugs (including other lipid-lowering therapies), and higher LIVALO dosage [see Dosage and Administration (2.2), Drug Interactions (7), and Use in Specific Populations (8.5, 8.6)]. Dosages of LIVALO greater than 4 mg once daily were associated with an increased risk for severe myopathy in premarketing clinical studies. The maximum recommended dose of LIVALO is 4 mg once daily.

Steps to Prevent or Reduce the Risk of Myopathy and Rhabdomyolysis

LIVALO is contraindicated in patients taking cyclosporine and not recommended in patients taking gemfibrozil [see Contraindications (4) and Drug Interactions (7)]. There are LIVALO dosage restrictions for patients taking erythromycin or rifampin [see Dosage and Administration (2.4)]. The following drugs when used concomitantly with LIVALO may also increase the risk of myopathy and rhabdomyolysis: lipid-modifying dosages of niacin (>1grams/day), fibrates, and colchicine [see Drug Interactions (7)].

Discontinue LIVALO if markedly elevated CK levels occur or if myopathy is either diagnosed or suspected. Muscle symptoms and CK elevations may resolve if LIVALO is discontinued. Temporarily discontinue LIVALO in patients experiencing an acute or serious condition at high risk of developing renal failure secondary to rhabdomyolysis (e.g., sepsis; shock; severe hypovolemia; major surgery; trauma; severe metabolic, endocrine, or electrolyte disorders; or uncontrolled epilepsy).

Inform patients of the risk of myopathy and rhabdomyolysis when starting or increasing the LIVALO dosage. Instruct patients to promptly report any unexplained muscle pain, tenderness or weakness, particularly if accompanied by malaise or fever.

5.2 Immune-Mediated Necrotizing Myopathy

There have been rare reports of immune-mediated necrotizing myopathy (IMNM), an autoimmune myopathy, associated with statin use , including reports of recurrence when the same or a different statin was administered. IMNM is characterized by proximal muscle weakness and elevated serum creatine kinase that persist despite discontinuation of statin treatment; positive anti-HMG CoA reductase antibody; muscle biopsy showing necrotizing myopathy; and improvement with immunosuppressive agents. Additional neuromuscular and serologic testing may be necessary. Treatment with immunosuppressive agents may be required. Discontinue LIVALO if IMNM is suspected.

5.3 Hepatic Dysfunction

Increases in serum transaminases have been reported with LIVALO [see Adverse Reactions (6)]. In most cases, these changes appeared soon after initiation, were transient, were not accompanied by symptoms, and resolved or improved on continued therapy or after a brief interruption in therapy. There have been rare postmarketing reports of fatal and non-fatal hepatic failure in patients taking statins, including LIVALO.

Patients who consume substantial quantities of alcohol and/or have a history of liver disease may be at increased risk for hepatic injury.

Consider liver enzyme testing before the initiation of LIVALO and when clinically indicated thereafter. LIVALO is contraindicated in patients with acute liver failure or decompensated cirrhosis [see Contraindications (4)]. If serious hepatic injury with clinical symptoms and/or hyperbilirubinemia or jaundice occurs, promptly discontinue LIVALO.

5.4 Increases in HbA1c and Fasting Serum Glucose Levels

Increases in HbA1c and fasting serum glucose levels have been reported with statins, including LIVALO. Optimize lifestyle measures, including regular exercise, maintaining a healthy body weight, and making healthy food choices.

6 ADVERSE REACTIONS

The following serious adverse reactions are discussed in other sections of the labeling:

- Myopathy and Rhabdomyolysis [see Warnings and Precautions (5.1)]
- Immune-Mediated Necrotizing Myopathy [see Warning and Precautions (5.2)]
- Hepatic Dysfunction [see Warning and Precautions (5.3)]
- Increases in HbA1c and Fasting Serum Glucose Levels [see Warning and Precautions (5.4)].

6.1 Clinical Studies Experience

Because clinical studies are conducted under widely varying conditions, adverse reaction rates observed in the clinical studies of one drug cannot be directly compared to rates in the clinical studies of another drug and may not reflect the rates observed in practice.

Adverse Reactions in Adults with Primary Hyperlipidemia

In 10 controlled clinical studies and 4 subsequent open-label extension studies, 3,291 adult patients with primary hyperlipidemia were administered LIVALO 1 mg to 4 mg daily. The mean continuous exposure of pitavastatin (1 mg to 4 mg) was 36.7 weeks (median 51.1 weeks). The mean age of the patients was 60.9 years (range; 18 years – 89 years) and 52% were females. Approximately 93% of the patients were White, 7% were Asian/Indian, 0.2% were African American and 0.3% were Hispanic and other.

In controlled clinical studies and their open-label extensions, 3.9% (1 mg), 3.3% (2 mg), and 3.7% (4 mg) of LIVALO-treated patients were discontinued due to adverse reactions. The most common adverse reactions that led to treatment discontinuation were: elevated creatine phosphokinase (0.6% on 4 mg) and myalgia (0.5% on 4 mg).

Adverse reactions reported in ≥ 2% of patients in controlled clinical studies and at a rate greater than or equal to placebo are shown in Table 1. These studies had treatment duration of up to 12 weeks.

Table 1. Adverse Reactions (≥ 2% and ≥ placebo) in Adults with Primary Hyperlipidemia in Studies up to 12 Weeks
Adverse Reactions | Placebo (n= 208) % | LIVALO 1 mg (n=309) % | LIVALO 2 mg (n=951) % | LIVALO 4 mg (n=1540) %
Myalgia | 1.4 | 1.9 | 2.8 | 3.1
Constipation | 1.9 | 3.6 | 1.5 | 2.2
Diarrhea | 1.9 | 2.6 | 1.5 | 1.9
Back pain | 2.9 | 3.9 | 1.8 | 1.4
Pain in extremity | 1.9 | 2.3 | 0.6 | 0.9

Other adverse reactions reported from clinical studies were arthralgia, headache, influenza, and nasopharyngitis.

Hypersensitivity reactions including rash, pruritus, and urticaria have been reported with LIVALO.

The following laboratory abnormalities have been reported: elevated creatine phosphokinase, transaminases, alkaline phosphatase, bilirubin, and glucose.

Adverse Reactions in Adult HIV-Infected Patients with Dyslipidemia

In a double-blind, randomized, controlled, 52-week trial, 252 HIV-infected patients with dyslipidemia were treated with either LIVALO 4 mg once daily (n=126) or another statin (n=126). All patients were taking antiretroviral therapy (excluding darunavir) and had HIV-1 RNA less than 200 copies/mL and CD4 count greater than 200 cell/µL for at least 3 months prior to randomization. The safety profile of LIVALO was generally consistent with that observed in the clinical trials described above. One patient (0.8%) treated with LIVALO had a peak creatine phosphokinase value exceeding 10 times the upper limit of normal (ULN), which resolved spontaneously. Four patients (3%) treated with LIVALO had at least one ALT value exceeding 3 times but less than 5 times the ULN, none of which led to drug discontinuation. Virologic failure was reported for four patients (3%) treated with LIVALO, defined as a confirmed measurement of HIV-1 RNA exceeding 200 copies/mL that was also more than a 2-fold increase from baseline.

Adverse Reactions in Pediatric Patients Aged 8 Years and Older with HeFH

In a 12-week, double-blind, placebo-controlled trial of LIVALO 1 mg, 2 mg, and 4 mg once daily in 82 pediatric patients 8 years to 16 years of age with HeFH and a 52-week open-label trial in 85 pediatric patients with HeFH, the safety profile was similar to that observed in the adult population.

6.2 Postmarketing Experience

The following adverse reactions have been identified during postapproval use of LIVALO. Because these reactions are reported voluntarily from a population of uncertain size, it is not always possible to reliably estimate their frequency or establish a causal relationship to drug exposure.

Gastrointestinal disorders: abdominal discomfort, abdominal pain, dyspepsia, nausea
General disorders: asthenia, fatigue, malaise, dizziness
Hepatobiliary disorders: hepatitis, jaundice, fatal and non-fatal hepatic failure
Immune system disorders: angioedema, immune-mediated necrotizing myopathy associated with statin use
Metabolism and nutrition disorders: increases in HbA1c, fasting serum glucose levels
Musculoskeletal and connective tissue disorders: muscle spasms, myopathy, rhabdomyolysis
Nervous system disorders: hypoesthesia, peripheral neuropathy. There have been rare reports of new onset or exacerbation of myasthenia gravis, including ocular myasthenia, and reports of recurrence when the same or a different statin was administered. Rare reports of cognitive impairment (e.g., memory loss, forgetfulness, amnesia, memory impairment, confusion) associated with statin use. Cognitive impairment was generally nonserious, and reversible upon statin discontinuation, with variable times to symptom onset (1 day to years) and symptom resolution (median of 3 weeks).
Psychiatric disorders: insomnia, depression
Reproductive system and breast disorders: erectile dysfunction
Respiratory, thoracic and mediastinal disorders: interstitial lung disease
Skin and subcutaneous tissue disorders: lichen planus

7 DRUG INTERACTIONS

Table 2 includes a list of drugs that increase the risk of myopathy and rhabdomyolysis when administered concomitantly with LIVALO and instructions for preventing or managing drug interactions [see Warnings and Precautions (5.1), Clinical Pharmacology (12.3)].

Table 2: Drug Interactions that Increase the Risk of Myopathy and Rhabdomyolysis with LIVALO
Cyclosporine
Clinical Impact: | Cyclosporine significantly increases pitavastatin exposure and increases the risk of myopathy and rhabdomyolysis.
Intervention: | Concomitant use of cyclosporine with LIVALO is contraindicated [see Contraindications (4)].
Gemfibrozil
Clinical Impact: | Gemfibrozil may cause myopathy when given alone. The risk of myopathy and rhabdomyolysis is increased with concomitant use of gemfibrozil with statins, including LIVALO.
Intervention: | Avoid concomitant use of gemfibrozil with LIVALO.
Erythromycin
Clinical Impact: | Erythromycin significantly increases pitavastatin exposure and increases the risk of myopathy and rhabdomyolysis.
Intervention: | In patients taking erythromycin, do not exceed LIVALO 1 mg once daily [see Dosage and Administration (2.4)].
Rifampin
Clinical Impact: | Rifampin significantly increases peak pitavastatin exposure and increases the risk of myopathy and rhabdomyolysis.
Intervention: | In patients taking rifampin, do not exceed LIVALO 2 mg once daily [see Dosage and Administration (2.4)].
Fibrates
Clinical Impact: | Fibrates may cause myopathy when given alone. The risk of myopathy and rhabdomyolysis is increased with concomitant use of fibrates with statins, including LIVALO.
Intervention: | Consider if the benefit of using fibrates concomitantly with LIVALO outweighs the increased risk of myopathy and rhabdomyolysis.
Niacin
Clinical Impact: | The risk of myopathy and rhabdomyolysis may be increased with concomitant use of lipid-modifying doses (≥1 g/day) of niacin with LIVALO.
Intervention: | Consider if the benefit of using lipid-modifying doses (≥1 g/day) of niacin concomitantly with LIVALO outweighs the increased risk of myopathy and rhabdomyolysis.
Colchicine
Clinical Impact: | Cases of myopathy and rhabdomyolysis have been reported with concomitant use of colchicine with statins, including LIVALO.
Intervention: | Consider the risk/benefit of concomitant use of colchicine with LIVALO.

8 USE IN SPECIFIC POPULATIONS

8.1 Pregnancy

Risk Summary

Discontinue LIVALO when pregnancy is recognized. Alternatively, consider the ongoing therapeutic needs of the individual patient.

LIVALO decreases synthesis of cholesterol and possibly other biologically active substances derived from cholesterol; therefore, LIVALO may cause fetal harm when administered to pregnant patients based on the mechanism of action [see Clinical Pharmacology (12.1)]. In addition, treatment of hyperlipidemia is not generally necessary during pregnancy. Atherosclerosis is a chronic process and the discontinuation of lipid-lowering drugs during pregnancy should have little impact on the outcome of long-term therapy of primary hyperlipidemia for most patients.

Available data from case series and prospective and retrospective observational cohort studies over decades of use with statins in pregnant women have not identified a drug-associated risk of major congenital malformations. Published data from prospective and retrospective observational cohort studies with statin use in pregnant women are insufficient to determine if there is a drug associated risk of miscarriage (see Data).

In animal reproduction studies, no embryo-fetal toxicity or congenital malformations were observed in pregnant rats and rabbits orally administered pitavastatin during the period of organogenesis at doses which were 22 and 4 times, respectively, the human exposure at the maximum recommended human dosage (MRHD) of 4 mg, based on AUC [see Data].

The estimated background risk of major birth defects and miscarriage for the indicated population is unknown. Adverse outcomes in pregnancy occur regardless of the health of the mother or the use of medications. In the U.S. general population, the estimated background risk of major birth defects and miscarriage in clinically recognized pregnancies is 2-4% and 15-20%, respectively.

Data

Human Data

A Medicaid cohort linkage study of 1152 statin-exposed pregnant women compared to 886,996 controls did not find a significant teratogenic effect from maternal use of statins in the first trimester of pregnancy, after adjusting for potential confounders – including maternal age, diabetes mellitus, hypertension, obesity, and alcohol and tobacco use – using propensity score-based methods. The relative risk of congenital malformations between the group with statin use and the group with no statin use in the first trimester was 1.07 (95% confidence interval 0.85 to 1.37) after controlling for confounders, particularly pre-existing diabetes mellitus. There were also no statistically significant increases in any of the organ-specific malformations assessed after accounting for confounders. In the majority of pregnancies, statin treatment was initiated prior to pregnancy and was discontinued at some point in the first trimester when pregnancy was identified. Study limitations include reliance on physician coding to define the presence of a malformation, lack of control for certain confounders such as body mass index, use of prescription dispensing as verification for the use of a statin, and lack of information on non-live births.

Animal Data

Embryo-fetal developmental studies were conducted in pregnant rats administered 3, 10, 30 mg/kg/day pitavastatin by oral gavage during organogenesis (gestation days 7-17). No adverse effects were observed at 3 mg/kg/day, systemic exposures 22 times human systemic exposure at 4 mg/day based on AUC.

Embryo-fetal developmental studies were conducted in pregnant rabbits administered 0.1, 0.3, 1 mg/kg/day pitavastatin by oral gavage during the period of fetal organogenesis (gestation days 6-18). Maternal toxicity consisting of reduced body weight and abortion was observed at all doses tested (4 times human systemic exposure at 4 mg/day based on AUC).

In perinatal/postnatal studies in pregnant rats given oral gavage doses of pitavastatin at 0.1, 0.3, 1, 3, 10, 30 mg/kg/day from organogenesis through weaning (gestation day 17 to lactation day 21), maternal toxicity consisting of mortality at ≥0.3 mg/kg/day and impaired lactation at all doses contributed to the decreased survival of neonates in all dose groups (0.1 mg/kg/day represents approximately 1 time human systemic exposure at 4 mg/day dose based on AUC).

Reproductive toxicity studies have shown that pitavastatin crosses the placenta in rats and is found in fetal tissues at ≤36% of maternal plasma concentrations following a single dose of 1 mg/kg/day during gestation (at the end of organogenesis).

8.2 Lactation

Risk Summary

There is no available information about the prescence of pitavastatin in human or animal milk, the effects of the drug on the breastfed infant, or the effects of the drug on milk production. However, it has been shown that another drug in this class passes into human milk. Statins, including LIVALO, decrease cholesterol synthesis and possibly the synthesis of other biologically active substances derived from cholesterol and may cause harm to the breastfed infant.

Because of the potential for serious adverse reactions in a breastfed infant, based upon the mechanism of action, advise patients that breastfeeding is not recommended during treatment with LIVALO. [see Use in Specific Populations (8.1), Clinical Pharmacology (12.1)]

8.4 Pediatric Use

The safety and effectiveness of LIVALO as an adjunctive therapy to diet to reduce elevated LDL-C in pediatric patients aged 8 years and older with HeFH have been established. Use of LIVALO for this indication is supported by a 12-week, double-blind, placebo-controlled trial in 82 pediatric patients 8 to 16 years of age with HeFH [see Clinical Studies (14.2)] and a 52-week open-label trial in 85 pediatric patients with HeFH.

The safety and effectiveness of LIVALO have not been established in pediatric patients younger than 8 years of age with HeFH or in pediatric patients with other types of hyperlipidemia (other than HeFH).

8.5 Geriatric Use

In controlled clinical studies, 1,209 (43%) patients were 65 years and older. No overall differences in safety or effectiveness were observed between these patients and younger patients.

Advanced age (≥65 years) is a risk factor for LIVALO-associated myopathy and rhabdomyolysis. Dose selection for a geriatric patient should be cautious, reognizing the greater frequency of decreased hepatic, renal, or cardiac function, and of concomitant disease or other drug therapy and the higher risk of myopathy. Monitor geriatric patients receiving LIVALO for the increased risk of myopathy [see Warnings and Precautions (5.1)].

8.6 Renal Impairment

Renal impairment is a risk factor for myopathy and rhabdomyolysis. Monitor all patients with renal impairment for development of myopathy. Due to the risk of myopathy, a dosage modification of LIVALO is recommended for patients with moderate and severe renal impairment (estimated glomerular filtration rate 30 – 59 mL/min/1.73 m^2 and 15 – 29 mL/min/1.73 m^2, respectively), as well as end-stage renal disease receiving hemodialysis. [see Dosage and Administration (2.3), Warnings and Precautions (5.1), Clinical Pharmacology (12.3)].

8.7 Hepatic Impairment

LIVALO is contraindicated in patients with active liver failure or decompensated cirrhosis [see Contraindications (4), Warnings and Precautions (5.3)].

10 OVERDOSAGE

No specific treatment for LIVALO overdose is known. Contact Poison Control (1-800-222-1222) for latest recommendations. Hemodialysis is unlikely to be of benefit due to high protein binding ratio of LIVALO.

11 DESCRIPTION

LIVALO (pitavastatin) tablets for oral use is an HMG-CoA reductase inhibitor.

The chemical name for pitavastatin is (+)monocalcium bis{(3R, 5S, 6E)-7-[2-cyclopropyl-4-(4-fluorophenyl)-3-quinolyl]-3,5-dihydroxy-6-heptenoate}. The structural formula is:

The empirical formula for pitavastatin is C50H46CaF2N2O8 and the molecular weight is 880.98. Pitavastatin is odorless and occurs as white to pale-yellow powder. It is freely soluble in pyridine, chloroform, dilute hydrochloric acid, and tetrahydrofuran, soluble in ethylene glycol, sparingly soluble in octanol, slightly soluble in methanol, very slightly soluble in water or ethanol, and practically insoluble in acetonitrile or diethyl ether. Pitavastatin is hygroscopic and slightly unstable in light.

Each film-coated tablet of LIVALO contains 1 mg, 2 mg, or 4 mg of pitavastatin, which is equivalent to 1.045 mg, 2.09 mg, or 4.18 mg, respectively, of pitavastatin calcium and the following inactive ingredients: hypromellose, lactose monohydrate, low substituted hydroxypropylcellulose, magnesium aluminometasilicate, and magnesium stearate. The film coating contains the following inactive ingredients: colloidal anhydrous silica, hypromellose, titanium dioxide, and triethyl citrate.

12 CLINICAL PHARMACOLOGY

12.1 Mechanism of Action

Pitavastatin is an inhibitor of 3-hydroxy-3-methylglutaryl-coenzyme A (HMG-CoA) reductase, the enzyme that catalyzes the conversion of HMG-CoA to mevalonate, a rate-limiting step in the biosynthetic pathway for cholesterol. As a result, the expression of LDL-receptors followed by the uptake of LDL from blood to liver is accelerated and then the plasma TC decreases. Sustained inhibition of cholesterol synthesis in the liver also decreases levels of very low density lipoproteins.

12.2 Pharmacodynamics

Cardiac Electrophysiology

In a randomized, double-blind, placebo-controlled, 4-way parallel, active-comparator study with moxifloxacin in 174 healthy participants, LIVALO was not associated with clinically meaningful prolongation of the QTc interval or heart rate at daily doses up to 16 mg (4 times the recommended maximum dose of 4 mg daily).

12.3 Pharmacokinetics

Absorption

Pitavastatin peak plasma concentrations are achieved about 1 hour after oral administration. Both Cmax and AUC0-inf increased in an approximately dose-proportional manner for single LIVALO doses from 1 mg to 24 mg once daily. The absolute bioavailability of pitavastatin oral solution is 51%. The Cmax and AUC of pitavastatin did not differ following evening or morning drug administration. In healthy volunteers receiving 4 mg pitavastatin, the percent change from baseline for LDL-C following evening dosing was slightly greater than that following morning dosing. Pitavastatin was absorbed in the small intestine but very little in the colon.

Effect of Food

Administration of LIVALO with a high fat meal (50% fat content) decreases pitavastatin Cmax by 43% but does not significantly reduce pitavastatin AUC.

Distribution

Pitavastatin is more than 99% protein bound in human plasma, mainly to albumin and alpha 1-acid glycoprotein, and the mean volume of distribution is approximately 148 L.

Elimination

Metabolism

The principal route of pitavastatin metabolism is glucuronidation via liver uridine 5'-diphosphate glucuronosyltransferase (UGT) with subsequent formation of pitavastatin lactone. There is only minimal metabolism by the cytochrome P450 system. Pitavastatin is marginally metabolized by CYP2C9 and to a lesser extent by CYP2C8. The major metabolite in human plasma is the lactone, which is formed via an ester-type pitavastatin glucuronide conjugate by UGTs (UGT1A3 and UGT2B7).

Excretion

A mean of 15% of radioactivity of orally administered, single 32 mg ^14C-labeled pitavastatin dose was excreted in urine, whereas a mean of 79% of the dose was excreted in feces within 7 days. The mean plasma elimination half-life is approximately 12 hours.

Specific Populations

Geriatric Patients

In a pharmacokinetic study which compared healthy young and geriatric (≥65 years) volunteers, pitavastatin Cmax and AUC were 10 and 30% higher, respectively, in the geriatric patients [see Use in Specific Populations (8.4)]

Pediatric Patients

A 12-week study in pediatric patients 8 to 16 years of age treated with pitavastatin 1 mg, 2 mg and 4 mg administered once daily, showed a dose-dependent increase in pitavastatin plasma concentrations at trough (for 2 mg and 4 mg doses) and 1 hour post dose. A dose-dependent increase in pitavastatin lactone plasma concentrations was observed at trough and 1 hour post dose.

Male and Female Patients

In a pharmacokinetic study, which compared healthy male and female volunteers, pitavastatin Cmax and AUC were 60 and 54% higher, respectively in females.

Racial or Ethnic Groups

In pharmacokinetic studies pitavastatin Cmax and AUC were 21 and 5% lower, respectively in Black or African American healthy volunteers compared with those of White healthy volunteers. In pharmacokinetic comparison between White volunteers and Japanese volunteers, there were no significant differences in Cmax and AUC.

Patients with Renal Impairment

In patients with moderate renal impairment (estimated glomerular filtration rate of 30 – 59 mL/min/1.73 m^2) and end stage renal disease receiving hemodialysis, pitavastatin AUC0-inf is 102% and 86% higher than those of healthy volunteers, respectively, while pitavastatin Cmax is 60% and 40% higher than those of healthy volunteers, respectively. Patients received hemodialysis immediately before pitavastatin dosing and did not undergo hemodialysis during the pharmacokinetic study. Hemodialysis patients have 33% and 36% increases in the mean unbound fraction of pitavastatin as compared to healthy volunteers and patients with moderate renal impairment, respectively [see Use in Specific Populations (8.5)].

In another pharmacokinetic study, patients with severe renal impairment (estimated glomerular filtration rate 15 – 29 mL/min/1.73 m^2) not receiving hemodialysis were administered a single dose of LIVALO 4 mg. The AUC0-inf and the Cmax were 36% and 18% higher, respectively, compared with those of healthy volunteers. For both patients with severe renal impairment and healthy volunteers, the mean percentage of protein-unbound pitavastatin was approximately 0.6% [see Use in Specific Populations (8.5)].

The effect of mild renal impairment on pitavastatin exposure has not been studied.

Patients with Hepatic Impairment

The disposition of pitavastatin was compared in healthy volunteers and patients with various degrees of hepatic impairment. Pitavastatin Cmax and AUCinf in patients with moderate hepatic impairment (Child-Pugh B disease) was 2.7-fold and 3.8-fold higher, respectively as compared to healthy volunteers. In patients with mild hepatic impairment (Child-Pugh A disease), pitavastatin Cmax and AUCinf were 30% and 60% higher as compared to healthy volunteers. Mean pitavastatin half-life for moderate hepatic impairment, mild hepatic impairment, and healthy volunteers were 15, 10, and 8 hours, respectively [see Contraindications (4), Warnings and Precautions (5.3)].

Drug Interaction Studies

Warfarin

The steady-state pharmacodynamics (international normalized ratio [INR] and prothrombin time [PT]) and pharmacokinetics of warfarin in healthy volunteers were unaffected by the coadministration of LIVALO 4 mg daily.

Table 3 presents the effect of coadministered drugs on pitavastatin systemic exposure:

Table 3. Effect of Coadministered Drugs on Pitavastatin Systemic Exposure
Coadministered drug | Dosage regimen | Change in AUC [Data presented as x-fold change represent the ratio between coadministration and pitavastatin alone (i.e., 1-fold = no change). Data presented as % change represent % difference relative to pitavastatin alone (i.e., 0% = no change).] | Change in Cmax
Cyclosporine | Pitavastatin 2 mg QD for 6 days + cyclosporine 2 mg/kg on Day 6 | ↑ 4.6 fold [Considered clinically significant [see Dosage and Administration (2.4),Drug Interactions (7)]] | ↑ 6.6 fold
Erythromycin | Pitavastatin 4 mg single dose on Day 4 + erythromycin 500 mg 4 times daily for 6 days | ↑ 2.8 fold | ↑ 3.6 fold
Rifampin | Pitavastatin 4 mg QD + rifampin 600 mg QD for 5 days | ↑ 29% | ↑ 2.0 fold
Atazanavir | Pitavastatin 4 mg QD + atazanavir 300 mg daily for 5 days | ↑ 31% | ↑ 60%
Darunavir/Ritonavir | Pitavastatin 4mg QD on Days 1-5 and 12-16 + darunavir/ritonavir 800mg/100 mg QD on Days 6-16 | ↓ 26% | ↓ 4%
Lopinavir/Ritonavir | Pitavastatin 4 mg QD on Days 1-5 and 20-24 + lopinavir/ritonavir 400 mg/100 mg BID on Days 9 – 24 | ↓ 20% | ↓4 %
Gemfibrozil | Pitavastatin 4 mg QD + gemfibrozil 600 mg BID for 7 days | ↑ 45% | ↑ 31%
Fenofibrate | Pitavastatin 4 mg QD + fenofibrate 160 mg QD for 7 days | ↑18% | ↑ 11%
Ezetimibe | Pitavastatin 2 mg QD + ezetimibe 10 mg for 7 days | ↓ 2% | ↓0.2%
Enalapril | Pitavastatin 4 mg QD + enalapril 20 mg daily for 5 days | ↑ 6% | ↓ 7%
Digoxin | Pitavastatin 4 mg QD + digoxin 0.25 mg for 7 days | ↑ 4% | ↓ 9%
Diltiazem LA | Pitavastatin 4 mg QD on Days 1-5 and 11-15 and diltiazem LA 240 mg on Days 6-15 | ↑10% | ↑15%
Grapefruit Juice | Pitavastatin 2 mg single dose on Day 3 + grapefruit juice for 4 days | ↑ 15% | ↓ 12%
Itraconazole | Pitavastatin 4 mg single dose on Day 4 + itraconazole 200 mg daily for 5 days | ↓ 23% | ↓ 22%
BID = twice daily; QD = once daily; LA = Long Acting

Table 4 presents the effect of pitavastatin coadministration on systemic exposure of other drugs:

Table 4. Effect of Pitavastatin Coadministration on Systemic Exposure to Other Drugs
Coadministered drug | Dosage regimen |  | Change in AUC [Data presented as % change represent % difference relative to the investigated drug alone (i.e., 0% = no change).] | Change in Cmax
Atazanavir | Pitavastatin 4 mg QD + atazanavir 300 mg daily for 5 days |  | ↑ 6% | ↑ 13%
Darunavir | Pitavastatin 4mg QD on Days 1-5 and 12-16 + darunavir/ritonavir 800mg/100 mg QD on Days 6-16 |  | ↑ 3% | ↑ 6%
Lopinavir | Pitavastatin 4 mg QD on Days 1-5 and 20-24 + lopinavir/ritonavir 400 mg/100 mg BID on Days 9 – 24 |  | ↓ 9% | ↓ 7%
Ritonavir | Pitavastatin 4 mg QD on Days 1-5 and 20-24 + lopinavir/ritonavir 400 mg/100 mg BID on Days 9 – 24 |  | ↓ 11% | ↓ 11%
Ritonavir | Pitavastatin 4mg QD on Days 1-5 and 12-16 + darunavir/ritonavir 800mg/100 mg QD on Days 6-16 |  | ↑ 8% | ↑ 2%
Enalapril | Pitavastatin 4 mg QD + enalapril 20 mg daily for 5 days | Enalapril | ↑ 12% | ↑ 12%
Enalapril | Pitavastatin 4 mg QD + enalapril 20 mg daily for 5 days | Enalaprilat | ↓ 1% | ↓ 1%
Warfarin | Individualized maintenance dose of warfarin (2 - 7 mg) for 8 days + pitavastatin 4 mg QD for 9 days | R-warfarin | ↑ 7% | ↑ 3%
Warfarin | Individualized maintenance dose of warfarin (2 - 7 mg) for 8 days + pitavastatin 4 mg QD for 9 days | S-warfarin | ↑ 6% | ↑ 3%
Ezetimibe | Pitavastatin 2 mg QD + ezetimibe 10 mg for 7 days |  | ↑ 9% | ↑ 2%
Digoxin | Pitavastatin 4 mg QD + digoxin 0.25 mg for 7 days |  | ↓ 3% | ↓ 4%
Diltiazem LA | Pitavastatin 4 mg QD on Days 1-5 and 11-15 and diltiazem LA 240 mg on Days 6-15 |  | ↓ 2% | ↓ 7%
Rifampin | Pitavastatin 4 mg QD + rifampin 600 mg QD for 5 days |  | ↓ 15% | ↓ 18%
BID = twice daily; QD = once daily; LA = Long Acting

13 NONCLINICAL TOXICOLOGY

13.1 Carcinogenesis, Mutagenesis, Impairment of Fertility

In a 92-week carcinogenicity study in mice given pitavastatin, at the maximum tolerated dose of 75 mg/kg/day with systemic maximum exposures (AUC) 26 times the clinical maximum exposure at 4 mg daily, there was an absence of drug-related tumors.

In a 92-week carcinogenicity study in rats given pitavastatin at 1, 5, 25 mg/kg/day by oral gavage there was a significant increase in the incidence of thyroid follicular cell tumors at 25 mg/kg/day, which represents 295 times human systemic exposures based on AUC at the 4 mg daily maximum human dose.

In a 26-week transgenic mouse (Tg rasH2) carcinogenicity study where animals were given pitavastatin at 30, 75, and 150 mg/kg/day by oral gavage, no clinically significant tumors were observed.

Pitavastatin was not mutagenic in the Ames test with Salmonella typhimurium and Escherichia coli with and without metabolic activation, the micronucleus test following a single administration in mice and multiple administrations in rats, the unscheduled DNA synthesis test in rats, and a Comet assay in mice. In the chromosomal aberration test, clastogenicity was observed at the highest doses tested, which also elicited high levels of cytotoxicity.

Pitavastatin had no adverse effects on male and female rat fertility at oral doses of 10 and 30 mg/kg/day, respectively, at systemic exposures 56- and 354-times clinical exposure at 4 mg daily based on AUC.

Pitavastatin treatment in rabbits resulted in mortality in males and females given 1 mg/kg/day (30-times clinical systemic exposure at 4 mg daily based on AUC) and higher during a fertility study. Although the cause of death was not determined, rabbits had gross signs of renal toxicity (kidneys whitened) indicative of possible ischemia. Lower doses (15-times human systemic exposure) did not show significant toxicity in adult males and females. However, decreased implantations, increased resorptions, and decreased viability of fetuses were observed.

14 CLINICAL STUDIES

Primary Hyperlipidemia in Adults

Study with Atorvastatin (Study 301)

LIVALO was compared with atorvastatin calcium tablets (referred to as atorvastatin) in a randomized, multicenter, double-blind, double-dummy, active-controlled, non-inferiority study of 817 adult patients with primary hyperlipidemia or mixed dyslipidemia. Patients entered a 6- to 8-week wash-out/dietary lead-in period and then were randomized to a 12-week treatment with either LIVALO or atorvastatin (Table 5). Non-inferiority of pitavastatin to a given dose of atorvastatin was considered to be demonstrated if the lower bound of the 95% CI for the mean treatment difference was greater than -6% for the mean percent change in LDL-C.

Lipid results are shown in Table 5. For the percent change from baseline to endpoint in LDL-C, LIVALO was non-inferior to atorvastatin for the two pairwise comparisons: LIVALO 2 mg vs. atorvastatin 10 mg and LIVALO 4 mg vs. atorvastatin 20 mg. Mean treatment differences (95% CI) were 0% (-3%, 3%) and 1% (-2%, 4%), respectively.

Table 5. Lipid Response by Dose of LIVALO and Atorvastatin in Adult Patients with Primary Hyperlipidemia or Mixed Dyslipidemia in Study 301 (Mean % Change from Baseline at Week 12)
Treatment | N | LDL-C | Apo-B | TC | TG | HDL-C | non-HDL-C
LIVALO 2 mg daily | 315 | -38 | -30 | -28 | -14 | 4 | -35
LIVALO 4 mg daily | 298 | -45 | -35 | -32 | -19 | 5 | -41
Atorvastatin 10 mg daily | 102 | -38 | -29 | -28 | -18 | 3 | -35
Atorvastatin 20 mg daily | 102 | -44 | -36 | -33 | -22 | 2 | -41

Study with Simvastatin (Study 302)

LIVALO was compared with simvastatin tablets (referred to as simvastatin) in a randomized, multicenter, double-blind, double-dummy, active-controlled, non-inferiority study of 843 adult patients with primary hyperlipidemia or mixed dyslipidemia. Patients entered a 6- to 8-week wash-out/dietary lead-in period and then were randomized to a 12 week treatment with either LIVALO or simvastatin (Table 6). Non-inferiority of pitavastatin to a given dose of simvastatin was considered to be demonstrated if the lower bound of the 95% CI for the mean treatment difference was greater than -6% for the mean percent change in LDL-C.

Lipid results are shown in Table 6. For the percent change from baseline to endpoint in LDL-C, LIVALO was non-inferior to simvastatin for the two pairwise comparisons: LIVALO 2 mg vs. simvastatin 20 mg and LIVALO 4 mg vs. simvastatin 40 mg. Mean treatment differences (95% CI) were 4% (1%, 7%) and 1% (-2%, 4%), respectively.

Table 6. Lipid Response by Dose of LIVALO and Simvastatin in Adult Patients with Primary Hyperlipidemia or Mixed Dyslipidemia in Study 302 (Mean % Change from Baseline at Week 12)
Treatment | N | LDL-C | Apo-B | TC | TG | HDL-C | non-HDL-C
LIVALO 2 mg daily | 307 | -39 | -30 | -28 | -16 | 6 | -36
LIVALO 4 mg daily | 319 | -44 | -35 | -32 | -17 | 6 | -41
Simvastatin 20 mg daily | 107 | -35 | -27 | -25 | -16 | 6 | -32
Simvastatin 40 mg daily | 110 | -43 | -34 | -31 | -16 | 7 | -39

Study with Pravastatin in Geriatric Patients (Study 306)

LIVALO was compared with pravastatin sodium tablets (referred to as pravastatin) in a randomized, multicenter, double-blind, double-dummy, parallel group, active-controlled non-inferiority study of 942 geriatric patients (≥65 years) with primary hyperlipidemia or mixed dyslipidemia. Patients entered a 6- to 8-week wash-out/dietary lead-in period, and then were randomized to a once daily dose of LIVALO or pravastatin for 12 weeks (Table 7). Non-inferiority of LIVALO to a given dose of pravastatin was assumed if the lower bound of the 95% CI for the treatment difference was greater than -6% for the mean percent change in LDL-C.

Lipid results are shown in Table 7. LIVALO significantly reduced LDL-C compared to pravastatin as demonstrated by the following pairwise dose comparisons: LIVALO 1 mg vs. pravastatin 10 mg, LIVALO 2 mg vs. pravastatin 20 mg and LIVALO 4 mg vs. pravastatin 40 mg. Mean treatment differences (95% CI) were 9% (6%, 12%), 10% (7%, 13%) and 10% (7%, 13%), respectively.

Table 7. Lipid Response by Dose of LIVALO and Pravastatin in Geriatric Patients with Primary Hyperlipidemia or Mixed Dyslipidemia in Study 306 (Mean % Change from Baseline at Week 12)
Treatment | N | LDL-C | Apo-B | TC | TG | HDL-C | non-HDL-C
LIVALO 1 mg daily | 207 | -31 | -25 | -22 | -13 | 1 | -29
LIVALO 2 mg daily | 224 | -39 | -31 | -27 | -15 | 2 | -36
LIVALO 4 mg daily | 210 | -44 | -37 | -31 | -22 | 4 | -41
Pravastatin 10 mg daily | 103 | -22 | -17 | -15 | -5 | 0 | -20
Pravastatin 20 mg daily | 96 | -29 | -22 | -21 | -11 | -1 | -27
Pravastatin 40 mg daily | 102 | -34 | -28 | -24 | -15 | 1 | -32

Study with Simvastatin in Patients with ≥2 Risk Factors for Coronary Heart Disease (Study 304)

LIVALO was compared with simvastatin tablets (referred to as simvastatin) in a randomized, multicenter, double-blind, double-dummy, active-controlled, non-inferiority study of 351 adult patients with primary hyperlipidemia or mixed dyslipidemia with ≥2 risk factors for coronary heart disease. After a 6- to 8-week wash-out/dietary lead-in period, patients were randomized to a 12-week treatment with either LIVALO or simvastatin (Table 8). Non-inferiority of LIVALO to simvastatin was considered to be demonstrated if the lower bound of the 95% CI for the mean treatment difference was greater than -6% for the mean percent change in LDL-C.

Lipid results are shown in Table 8. LIVALO 4 mg was non-inferior to simvastatin 40 mg for percent change from baseline to endpoint in LDL-C. The mean treatment difference (95% CI) was 0% (-2%, 3%).

Table 8. Lipid Response by Dose of LIVALO and Simvastatin in Adult Patients with Primary Hyperlipidemia or Mixed Dyslipidemia with ≥2 Risk Factors for Coronary Heart Disease in Study 304 (Mean % Change from Baseline at Week 12)
Treatment | N | LDL-C | Apo-B | TC | TG | HDL-C | non-HDL-C
LIVALO 4 mg daily | 233 | -44 | -34 | -31 | -20 | 7 | -40
Simvastatin 40 mg daily | 118 | -44 | -34 | -31 | -15 | 5 | -39

Study with Atorvastatin in Patients with Type 2 Diabetes Mellitus (Study 305)

LIVALO was compared with atorvastatin calcium tablets (referred to as atorvastatin) in a randomized, multicenter, double-blind, double-dummy, parallel group, active-controlled, non-inferiority study of 410 adult patients with type 2 diabetes mellitus and mixed dyslipidemia. Patients entered a 6- to 8-week washout/dietary lead-in period and were randomized to a once daily dose of LIVALO or atorvastatin for 12 weeks. Non-inferiority of LIVALO was considered to be demonstrated if the lower bound of the 95% CI for the mean treatment difference was greater than -6% for the mean percent change in LDL-C.

Lipid results are shown in Table 9. The treatment difference (95% CI) for LDL-C percent change from baseline was -2% (-6.2%, 1.5%). The two treatment groups were not statistically different on LDL-C. However, the lower limit of the CI was -6.2%, slightly exceeding the -6% non-inferiority limit. The study failed to demonstrate that LIVALO was not significantly different than atorvastatin in lowering LDL-C in patients with type 2 diabetes mellitus and mixed dyslipidemia.

Table 9. Lipid Response by Dose of LIVALO and Atorvastatin in Adult Patients with Type 2 Diabetes Mellitus and Mixed Dyslipidemia in Study 305 (Mean % Change from Baseline at Week 12)
Treatment | N | LDL-C | Apo-B | TC | TG | HDL-C | non-HDL-C
LIVALO 4 mg daily | 274 | -41 | -32 | -28 | -20 | 7 | -36
Atorvastatin 20 mg daily | 136 | -43 | -34 | -32 | -27 | 8 | -40

The treatment differences in efficacy in LDL-C change from baseline between LIVALO and active controls (i.e., atorvastatin, simvastatin, or pravastatin) in the in the active-controlled studies described above are summarized in Figure 1.

Figure 1. Treatment Difference in Adjusted Mean Percent Change in LDL-C between LIVALO and the Comparator (Atorvastatin, Simvastatin, or Pravastatin)

NL=non-inferiority limit.

HeFH in Pediatric Patients

In a double-blind, placebo-controlled, 12-week trial, 82 pediatric patients (36 boys and 46 girls), 8 to 16 years of age with genetically confirmed HeFH, fasting low-density lipoprotein cholesterol (LDL-C) ≥190 mg/dL or LDL-C ≥160 mg/dL with an additional cardiovascular risk factor (male gender, a family history of premature CV disease, presence of low HDL (<45 mg/dL) or high TG (>150 mg/dL), presence of high lipoprotein (a) (>75 nmol/L), presence of type 2 diabetes mellitus or presence of hypertension) were randomized to LIVALO 1 mg, 2 mg, and 4 mg. Mean LDL-C at baseline was 235 mg/dL (range 160.5 mg/dL to 441mg/dL). Approximately 39% of patients were Tanner Stage 1 at baseline.

LIVALO significantly reduced plasma LDL-C, non-HDL-C, TC, and Apo-B compared to placebo. The reductions in LDL-C, Apo-B, TC, and non-HDL-C were dose dependent. There was no statistically significant improvement in HDL-C or TG at any LIVALO dose. See the lipid results in Table 10.

Table 10. Lipid Response in Pediatric Patients with HeFH (Mean % Change from Baseline at Week 12)
Treatment | N | LDL-C | Apo-B | TC | TG [Difference from placebo not statistically significant] [Median Percent Change from Baseline at Week 12] | HDL-C | non-HDL-C
Placebo | 19 | -1 | -3 | -1 | -3 | -1 | -1
LIVALO 1 mg daily | 20 | -21 | -20 | -16 | -14 | 7 | -21
LIVALO 2 mg daily | 24 | -30 | -25 | -25 | -15 | -3 | -29
LIVALO 4 mg daily | 19 | -38 | -28 | -30 | 5 | -2 | -36

16 HOW SUPPLIED/STORAGE AND HANDLING

LIVALO tablets are supplied as follows:

Tablet Strength | Package Size | Tablet Description | NDC
1 mg | Bottle of 90 | Round white film-coated tablet debossed "KC" on one face and "1" on the reverse | 66869-104-90
2 mg | Bottle of 90 | Round white film-coated tablet debossed "KC" on one face and "2" on the reverse | 66869-204-90
4 mg | Bottle of 90 | Round white film-coated tablet debossed "KC" on one face and "4" on the reverse | 66869-404-90

STORAGE AND HANDLING

Store at room temperature between 15°C and 30°C (59° to 86° F) [see USP]. Protect from light.

17 PATIENT COUNSELING INFORMATION

Myopathy and Rhabdomyolysis

Advise patients that LIVALO may cause myopathy and rhabdomyolysis. Inform patients that the risk is increased when taking certain types of medication and they should discuss all medication, both prescription and over the counter, with their healthcare provider. Instruct patients to promptly report any unexplained muscle pain, tenderness or weakness particularly if accompanied by malaise or fever [see Warnings and Precautions (5.1)].

Hepatic Dysfunction

Inform patients that LIVALO may cause liver enzyme elevations and possibly liver failure. Advise patients to promptly report fatigue, anorexia, right upper abdominal discomfort, dark urine or jaundice [see Warnings and Precautions (5.3)].

Increases in HbA1c and Fasting Serum Glucose Levels

Inform patients that increases in HbA1c and fasting serum glucose levels may occur with LIVALO. Encourage patients to optimize lifestyle measures, including regular exercise, maintaining a healthy body weight, and making healthy food choices [see Warnings and Precautions (5.4)].

Pregnancy

Advise pregnant patients and patients who become pregnant of the potential risk to a fetus. Advise patients to inform their healthcare provider of a known or suspected pregnancy to discuss if LIVALO should be discontinued [see Use in Specific Populations (8.1)].

Lactation

Advise patients that breastfeeding is not recommended during treatment with LIVALO [see Use in Specific Populations (8.2)].

Manufactured for:
Kowa Company, Limited Tokyo 103-8433 Japan
Manufactured by:
Patheon, Inc. Cincinnati, OH 45237 USA or by Kowa Company, LTD Nagoya, 462-0024 Japan
Marketed and Distributed by:
Kowa Pharmaceuticals America, Inc. Montgomery, AL 36117 USA

LIV-RA-0148 01/2024
LIVALO is a trademark of the Kowa group of companies.
© Kowa Pharmaceuticals America, Inc. (2009)

PRINCIPAL DISPLAY PANEL - 1 mg Tablet Bottle Label

NDC 66869-104-90

Livalo®
(pitavastatin) tablets

1 mg*

Rx Only

Kowa

Principal Display Panel - Bottle Label Livalo 2 mg

NDC 66869-204-90

Livalo®
(pitavastatin) tablets

2 mg*

Rx Only

LOGO-Kowa-LOGO

Principal display Panel - Bottle Label Livalo 4 mg

NDC 66869-404-90

Livalo®
(pitavastatin) tablets

4 mg*

Rx Only

LOGO-Kowa-LOGO

PACKAGE LABEL

Principal display Panel – Carton 2 mg

FREE SAMPLE NDC 66869-204-07

Livalo®

(pitavastatin) tablets

2 mg*

Rx Only

Contains 7 Tablets

LOGO-Kowa-LOGO

Professional Sample –

Not for Sale

*Each tablet contains:
Active ingredient: pitavastatin calcium 2.09 mg equivalent to pitavastatin 2 mg.

PACKAGE LABEL

Principal display Panel – Carton 4 mg

FREE SAMPLE NDC 66869-404-07

Livalo®
(pitavastatin) tablets

4 mg*

Rx Only

Contains 7 Tablets

LOGO-Kowa-LOGO

Professional Sample –
Not for Sale

*Each tablet contains:
Active ingredient: pitavastatin calcium 4.18 mg equivalent to pitavastatin 4 mg.